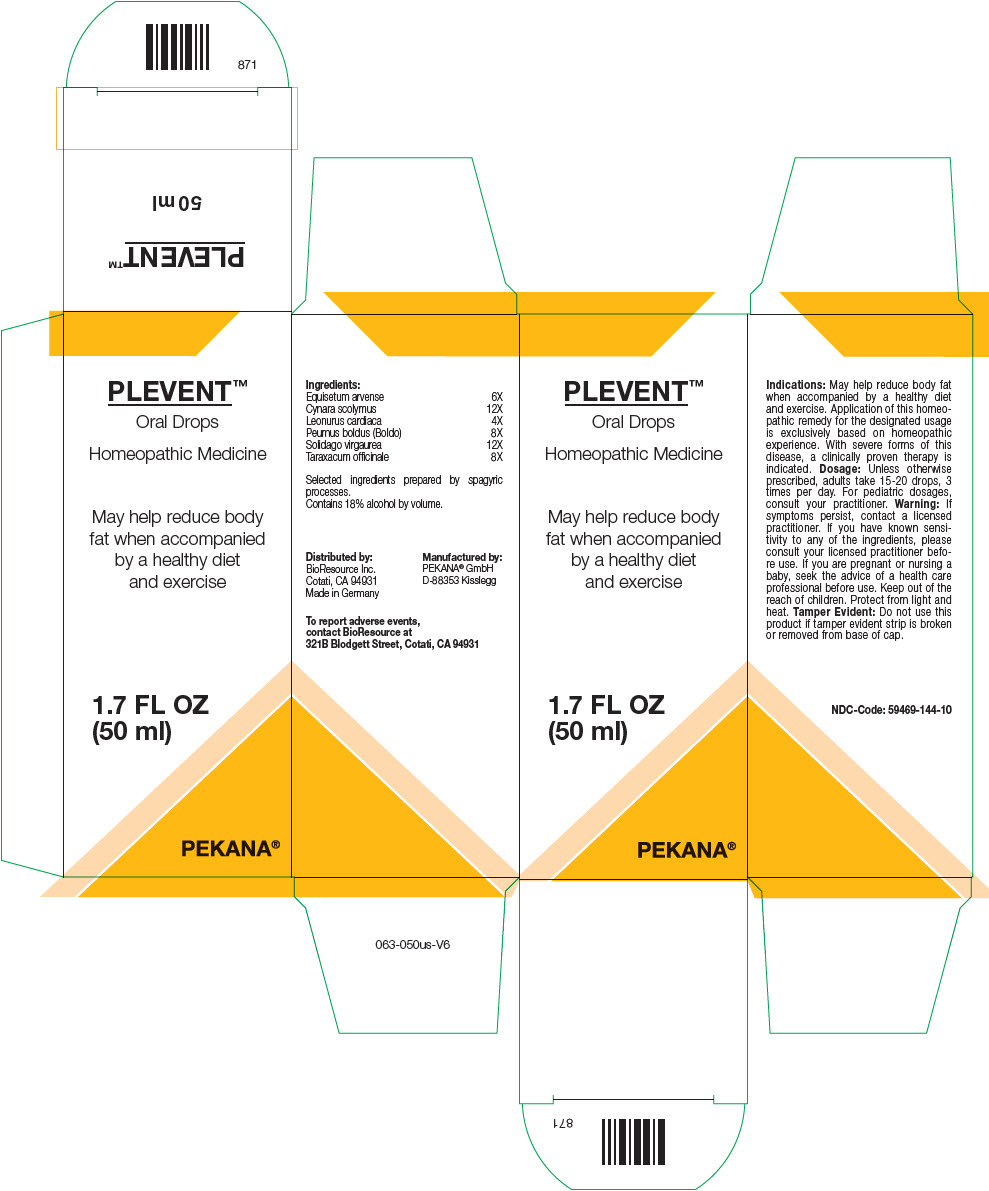 DRUG LABEL: PLEVENT
NDC: 59469-144 | Form: SOLUTION/ DROPS
Manufacturer: PEKANA Naturheilmittel GmbH
Category: homeopathic | Type: HUMAN OTC DRUG LABEL
Date: 20221216

ACTIVE INGREDIENTS: Peumus boldus Leaf 8 [hp_X]/50 mL; Cynara scolymus Whole 12 [hp_X]/50 mL; Equisetum arvense Top 6 [hp_X]/50 mL; Leonurus cardiaca Flowering Top 4 [hp_X]/50 mL; Solidago virgaurea Flowering Top 12 [hp_X]/50 mL; Taraxacum officinale Whole 8 [hp_X]/50 mL
INACTIVE INGREDIENTS: Water; Alcohol

PLEVENT™

ACTIVE INGREDIENT

Ingredients:
Equisetum arvense | 6X
Cynara scolymus | 12X
Leonurus cardiaca | 4X
Peumus boldus (Boldo) | 8X
Solidago virgaurea | 12X
Taraxacum officinale | 8X

Selected ingredients prepared by spagyric processes.

INACTIVE INGREDIENT

Contains 18% alcohol by volume.

Indications

PURPOSE

May help reduce body fat when accompanied by a healthy diet and exercise. Application of this homeopathic remedy for the designated usage is exclusively based on homeopathic experience. With severe forms of this disease, a clinically proven therapy is indicated.

Dosage

Unless otherwise prescribed, adults take 15-20 drops, 3 times per day. For pediatric dosages, consult your practitioner.

Warning

If symptoms persist, contact a licensed practitioner. If you have known sensitivity to any of the ingredients, please consult your licensed practitioner before use. If you are pregnant or nursing a baby, seek the advice of a health care professional before use.

Keep out of the reach of children.

STORAGE AND HANDLING

Protect from light and heat.

Tamper Evident

Do not use this product if tamper evident strip is broken or removed from base of cap.

QUESTIONS

To report adverse events, contact BioResource at 321B Blodgett Street, Cotati, CA 94931

Distributed by:
BioResource Inc.
Cotati, CA 94931

Manufactured by:
PEKANA® GmbH
D-88353 Kisslegg

PRINCIPAL DISPLAY PANEL - 50 ml Bottle Box

PLEVENT™
Oral Drops

Homeopathic Medicine

May help reduce body
fat when accompanied
by a healthy diet
and exercise

1.7 FL OZ
(50 ml)

PEKANA®